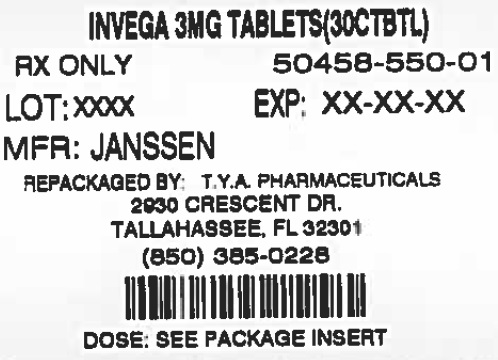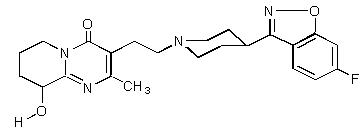 DRUG LABEL: INVEGA
NDC: 64725-0550 | Form: TABLET, EXTENDED RELEASE
Manufacturer: TYA Pharmaceuticals
Category: prescription | Type: HUMAN PRESCRIPTION DRUG LABEL
Date: 20140502

ACTIVE INGREDIENTS: paliperidone 3 mg/1 1
INACTIVE INGREDIENTS: CARNAUBA WAX; CELLULOSE ACETATE; POLYETHYLENE GLYCOLS; PROPYLENE GLYCOL; POVIDONES; SODIUM CHLORIDE; STEARIC ACID; BUTYLATED HYDROXYTOLUENE; HYPROMELLOSES; TITANIUM DIOXIDE; FERROSOFERRIC OXIDE; TRIACETIN; LACTOSE MONOHYDRATE

HIGHLIGHTS OF PRESCRIBING INFORMATION

These highlights do not include all the information needed to use INVEGA safely and effectively. See full prescribing information for INVEGA . INVEGA (paliperidone) Extended-Release Tablets Initial U.S. Approval: 2006®®
®

WARNING: INCREASED MORTALITY IN ELDERLY PATIENTS WITH DEMENTIA-RELATED PSYCHOSIS

See . full prescribing information for complete boxed warning

Elderly patients with dementia-related psychosis treated with antipsychotic drugs are at an increased risk of death. INVEGA is not approved for use in patients with dementia-related psychosis. ()® 5.1

1 INDICATIONS AND USAGE

INVEGA is an atypical antipsychotic agent indicated for®

Treatment of schizophrenia () 1.1

- Adults: Efficacy was established in three 6-week trials and one maintenance trial. () 14.1
- Adolescents (ages 12–17): Efficacy was established in one 6-week trial. () 14.1

Treatment of schizoaffective disorder as monotherapy and as an adjunct to mood stabilizers and/or antidepressants. () 1.2

- Efficacy was established in two 6-week trials in adult patients. () 14.2

2 DOSAGE AND ADMINISTRATION

 |  | Initial Dose | Recommended Dose | Maximum Dose
Schizophrenia - adults () 2.1 |  | 6 mg/day | 3 – 12 mg/day | 12 mg/day
Schizophrenia-adolescents () 2.1 | Weight < 51kg | 3 mg/day | 3 – 6 mg/day | 6 mg/day
Schizophrenia-adolescents () 2.1 | Weight ≥ 51kg | 3 mg/day | 3 – 12 mg/day | 12 mg/day
Schizoaffective disorder - adults () 2.2 |  | 6 mg/day | 3 – 12 mg/day | 12 mg/day

- Tablet should be swallowed whole and should not be chewed, divided, or crushed. () 2.3

3 DOSAGE FORMS AND STRENGTHS

Tablets: 1.5 mg, 3 mg, 6 mg, and 9 mg () 3

4 CONTRAINDICATIONS

Known hypersensitivity to paliperidone, risperidone, or to any components in the formulation. () 4

5 WARNINGS AND PRECAUTIONS

- An increased incidence of cerebrovascular adverse reactions (e.g. stroke, transient ischemic attack, including fatalities) has been seen in elderly patients with dementia- related psychoses treated with atypical antipsychotics. () Cerebrovascular Adverse Reactions:5.2
- Manage with immediate discontinuation of drug and close monitoring. () Neuroleptic Malignant Syndrome:5.3
- Increase in QT interval, avoid use with drugs that also increase QT interval and in patients with risk factors for prolonged QT interval. () QT Prolongation:5.4
- Discontinue drug if clinically appropriate. () Tardive Dyskinesia:5.5
- Atypical antipsychotic drugs have been associated with metabolic changes that may increase cardiovascular/ cerebrovascular risk. These metabolic changes include hyperglycemia, dyslipidemia, and weight gain. () Metabolic Changes:5.6
  - Monitor patients for symptoms of hyperglycemia including polydipsia, polyuria, polyphagia, and weakness. Monitor glucose regularly in patients with diabetes or at risk for diabetes. () Hyperglycemia and Diabetes Mellitus:5.6
  - Undesirable alterations have been observed in patients treated with atypical antipsychotics. () Dyslipidemia:5.6
  - Significant weight gain has been reported. Monitor weight gain. () Weight Gain:5.6
- Prolactin elevations occur and persist during chronic administration. () Hyperprolactinemia:5.7
- Obstructive symptoms may result in patients with gastrointestinal disease. () Gastrointestinal Narrowing:5.8
- Use with caution in patients with known cardiovascular or cerebrovascular disease and patients predisposed to hypotension. () Orthostatic Hypotension and Syncope:5.9
- has been reported with antipsychotics, including INVEGA . Patients with a history of a clinically significant low white blood cell count (WBC) or a drug-induced leukopenia/neutropenia should have their complete blood count (CBC) monitored frequently during the first few months of therapy and discontinuation of INVEGA should be considered at the first sign of a clinically significant decline in WBC in the absence of other causative factors. () Leukopenia, Neutropenia, and Agranulocytosis:®® 5.10
- Use caution when operating machinery. () Potential for Cognitive and Motor Impairment:5.11
- Use cautiously in patients with a history of seizures or with conditions that lower the seizure threshold. () Seizures:5.12
- Closely supervise high-risk patients. () Suicide:5.14

6 ADVERSE REACTIONS

Commonly observed adverse reactions (incidence ≥ 5% and at least twice that for placebo) were () 6

- Adults with schizophrenia: extrapyramidal symptoms, tachycardia, and akathisia.
- Adolescents with schizophrenia: somnolence, akathisia, tremor, dystonia, cogwheel rigidity, anxiety, weight increased, and tachycardia.
- Adults with schizoaffective disorder: extrapyramidal symptoms, somnolence, dyspepsia, constipation, weight increased, and nasopharyngitis.

To report SUSPECTED ADVERSE REACTIONS, contact Janssen Pharmaceuticals, Inc. at 1-800-JANSSEN (1-800-526-7736) or FDA at 1-800-FDA-1088 or www.fda.gov/medwatch

7 DRUG INTERACTIONS

- Centrally-acting drugs: Due to CNS effects, use caution in combination. Avoid alcohol. () 7.1
- Drugs that may cause orthostatic hypotension: An additive effect may be observed when co-administered with INVEGA . ()® 7.1
- Strong CYP3A4/P-glycoprotein (P-gp) inducers: It may be necessary to increase the dose of INVEGA when a strong inducer of both CYP3A4 and P-gp (e.g., carbamazepine) is co-administered. Conversely, on discontinuation of the strong inducer, it may be necessary to decrease the dose of INVEGA . ()®® 7.2
- Co-administration of divalproex sodium increased Cmax and AUC of paliperidone by approximately 50%. Adjust dose of INVEGA if necessary based on clinical assessment. ()® 7.2

8 USE IN SPECIFIC POPULATIONS

- Renal impairment: Dosing must be individualized according to renal function status. () 2.5
- Elderly: Same as for younger adults (adjust dose according to renal function status). () 2.4
- Nursing Mothers: The benefits of breastfeeding should be weighed against the unknown risks of infant exposure to paliperidone. () 8.3
- Pediatric Use: Safety and effectiveness in the treatment of schizophrenia not established in patients less than 12 years of age. Safety and effectiveness in the treatment of schizoaffective disorder not established in patients less than 18 years of age. () 8.4

FULL PRESCRIBING INFORMATION

WARNING: INCREASED MORTALITY IN ELDERLY PATIENTS WITH DEMENTIA-RELATED PSYCHOSIS

Elderly patients with dementia-related psychosis treated with antipsychotic drugs are at an increased risk of death. Analyses of 17 placebo-controlled trials (modal duration of 10 weeks), largely in patients taking atypical antipsychotic drugs, revealed a risk of death in drug-treated patients of between 1.6 to 1.7 times the risk of death in placebo-treated patients. Over the course of a typical 10-week controlled trial, the rate of death in drug-treated patients was about 4.5%, compared to a rate of about 2.6% in the placebo group. Although the causes of death were varied, most of the deaths appeared to be either cardiovascular (e.g., heart failure, sudden death) or infectious (e.g., pneumonia) in nature. Observational studies suggest that, similar to atypical antipsychotic drugs, treatment with conventional antipsychotic drugs may increase mortality. The extent to which the findings of increased mortality in observational studies may be attributed to the antipsychotic drug as opposed to some characteristic(s) of the patients is not clear. INVEGA (paliperidone) Extended-Release Tablets is not approved for the treatment of patients with dementia-related psychosis.® [see ] Warnings and Precautions (5.1)

1 INDICATIONS AND USAGE

1.1 Schizophrenia

INVEGA (paliperidone) Extended-Release Tablets are indicated for the treatment of schizophrenia .® [see ] Clinical Studies (14.1)

The efficacy of INVEGA in schizophrenia was established in three 6-week trials in adults and one 6-week trial in adolescents, as well as one maintenance trial in adults.®

1.2 Schizoaffective Disorder

INVEGA (paliperidone) Extended-Release Tablets are indicated for the treatment of schizoaffective disorder as monotherapy and an adjunct to mood stabilizers and/or antidepressant therapy .® [see ] Clinical Studies (14.2)

The efficacy of INVEGA in schizoaffective disorder was established in two 6-week trials in adults.®

2 DOSAGE AND ADMINISTRATION

2.1 Schizophrenia

Adults

The recommended dose of INVEGA (paliperidone) Extended-Release Tablets for the treatment of schizophrenia in adults is 6 mg administered once daily. Initial dose titration is not required. Although it has not been systematically established that doses above 6 mg have additional benefit, there was a general trend for greater effects with higher doses. This must be weighed against the dose-related increase in adverse reactions. Thus, some patients may benefit from higher doses, up to 12 mg/day, and for some patients, a lower dose of 3 mg/day may be sufficient. Dose increases above 6 mg/day should be made only after clinical reassessment and generally should occur at intervals of more than 5 days. When dose increases are indicated, increments of 3 mg/day are recommended. The maximum recommended dose is 12 mg/day.®

In a longer-term study, INVEGA has been shown to be effective in delaying time to relapse in patients with schizophrenia who were stabilized on INVEGA for 6 weeks . INVEGA should be prescribed at the lowest effective dose for maintaining clinical stability and the physician should periodically reevaluate the long-term usefulness of the drug in individual patients.®® [see ] Clinical Studies (14)®

Adolescents (12–17 years of age)

The recommended starting dose of INVEGA (paliperidone) Extended-Release Tablets for the treatment of schizophrenia in adolescents 12–17 years of age is 3 mg administered once daily. Initial dose titration is not required. Dose increases, if considered necessary, should be made only after clinical reassessment and should occur at increments of 3 mg/day at intervals of more than 5 days. Prescribers should be mindful that, in the adolescent schizophrenia study, there was no clear enhancement to efficacy at the higher doses, i.e., 6 mg for subjects weighing less than 51 kg and 12 mg for subjects weighing 51 kg or greater, while adverse events were dose-related.®

2.2 Schizoaffective Disorder

The recommended dose of INVEGA (paliperidone) Extended-Release Tablets for the treatment of schizoaffective disorder in adults is 6 mg administered once daily. Initial dose titration is not required. Some patients may benefit from lower or higher doses within the recommended dose range of 3 to 12 mg once daily. A general trend for greater effects was seen with higher doses. This trend must be weighed against dose-related increase in adverse reactions. Dosage adjustment, if indicated, should occur only after clinical reassessment. Dose increases, if indicated, generally should occur at intervals of more than 4 days. When dose increases are indicated, increments of 3 mg/day are recommended. The maximum recommended dose is 12 mg/day.®

2.3 Administration Instructions

INVEGA can be taken with or without food.®

INVEGA must be swallowed whole with the aid of liquids. Tablets should not be chewed, divided, or crushed. The medication is contained within a nonabsorbable shell designed to release the drug at a controlled rate. The tablet shell, along with insoluble core components, is eliminated from the body; patients should not be concerned if they occasionally notice in their stool something that looks like a tablet.®

2.4 Use with Risperidone

Concomitant use of INVEGA with risperidone has not been studied. Since paliperidone is the major active metabolite of risperidone, consideration should be given to the additive paliperidone exposure if risperidone is coadministered with INVEGA .®®

2.5 Dosage in Special Populations

Renal Impairment

Dosing must be individualized according to the patient's renal function status. For patients with mild renal impairment (creatinine clearance ≥ 50 mL/min to < 80 mL/min), the recommended initial dose of INVEGA is 3 mg once daily. The dose may then be increased to a maximum of 6 mg once daily based on clinical response and tolerability. For patients with moderate to severe renal impairment (creatinine clearance ≥ 10 mL/min to < 50 mL/min), the recommended initial dose of INVEGA is 1.5 mg once daily, which may be increased to a maximum of 3 mg once daily after clinical reassessment. As INVEGA has not been studied in patients with creatinine clearance below 10 mL/min, use is not recommended in such patients.®®® [See ] Clinical Pharmacology (12.3)

Hepatic Impairment

For patients with mild to moderate hepatic impairment, (Child-Pugh Classification A and B), no dose adjustment is recommended . INVEGA has not been studied in patients with severe hepatic impairment. [see ] Clinical Pharmacology (12.3)®

Elderly

Because elderly patients may have diminished renal function, dose adjustments may be required according to their renal function status. In general, recommended dosing for elderly patients with normal renal function is the same as for younger adult patients with normal renal function. For patients with moderate to severe renal impairment (creatinine clearance 10 mL/min to < 50 mL/min), the maximum recommended dose of INVEGA is 3 mg once daily .® [see ] Renal Impairment above

3 DOSAGE FORMS AND STRENGTHS

INVEGA Extended-Release Tablets are available in the following strengths and colors: 1.5 mg (orange-brown), 3 mg (white), 6 mg (beige), and 9 mg (pink). All tablets are capsule shaped and are imprinted with either "PAL 1.5", "PAL 3", "PAL 6", or "PAL 9".®

4 CONTRAINDICATIONS

Hypersensitivity reactions, including anaphylactic reactions and angioedema, have been observed in patients treated with risperidone and paliperidone. INVEGA (paliperidone) is a metabolite of risperidone and is therefore contraindicated in patients with a known hypersensitivity to either paliperidone or risperidone, or to any of the excipients in INVEGA .®®

5 WARNINGS AND PRECAUTIONS

5.1 Increased Mortality in Elderly Patients with Dementia-Related Psychosis

Elderly patients with dementia-related psychosis treated with antipsychotic drugs are at an increased risk of death. INVEGA (paliperidone) is not approved for the treatment of dementia-related psychosis .® [see ] Boxed Warning

5.2 Cerebrovascular Adverse Reactions, Including Stroke, in Elderly Patients With Dementia-Related Psychosis

In placebo-controlled trials with risperidone, aripiprazole, and olanzapine in elderly subjects with dementia, there was a higher incidence of cerebrovascular adverse reactions (cerebrovascular accidents and transient ischemic attacks) including fatalities compared to placebo-treated subjects. INVEGA was not marketed at the time these studies were performed. INVEGA is not approved for the treatment of patients with dementia-related psychosis .®® [see also and ] Boxed Warning Warnings and Precautions (5.1)

5.3 Neuroleptic Malignant Syndrome

A potentially fatal symptom complex sometimes referred to as Neuroleptic Malignant Syndrome (NMS) has been reported in association with antipsychotic drugs, including paliperidone. Clinical manifestations of NMS are hyperpyrexia, muscle rigidity, altered mental status, and evidence of autonomic instability (irregular pulse or blood pressure, tachycardia, diaphoresis, and cardiac dysrhythmia). Additional signs may include elevated creatine phosphokinase, myoglobinuria (rhabdomyolysis), and acute renal failure.

The diagnostic evaluation of patients with this syndrome is complicated. In arriving at a diagnosis, it is important to identify cases in which the clinical presentation includes both serious medical illness (e.g., pneumonia, systemic infection, etc.) and untreated or inadequately treated extrapyramidal signs and symptoms (EPS). Other important considerations in the differential diagnosis include central anticholinergic toxicity, heat stroke, drug fever, and primary central nervous system pathology.

The management of NMS should include: (1) immediate discontinuation of antipsychotic drugs and other drugs not essential to concurrent therapy; (2) intensive symptomatic treatment and medical monitoring; and (3) treatment of any concomitant serious medical problems for which specific treatments are available. There is no general agreement about specific pharmacological treatment regimens for uncomplicated NMS.

If a patient appears to require antipsychotic drug treatment after recovery from NMS, reintroduction of drug therapy should be closely monitored, since recurrences of NMS have been reported.

5.4 QT Prolongation

Paliperidone causes a modest increase in the corrected QT (QTc) interval. The use of paliperidone should be avoided in combination with other drugs that are known to prolong QTc including Class 1A (e.g., quinidine, procainamide) or Class III (e.g., amiodarone, sotalol) antiarrhythmic medications, antipsychotic medications (e.g., chlorpromazine, thioridazine), antibiotics (e.g., gatifloxacin, moxifloxacin), or any other class of medications known to prolong the QTc interval. Paliperidone should also be avoided in patients with congenital long QT syndrome and in patients with a history of cardiac arrhythmias.

Certain circumstances may increase the risk of the occurrence of torsade de pointes and/or sudden death in association with the use of drugs that prolong the QTc interval, including (1) bradycardia; (2) hypokalemia or hypomagnesemia; (3) concomitant use of other drugs that prolong the QTc interval; and (4) presence of congenital prolongation of the QT interval.

The effects of paliperidone on the QT interval were evaluated in a double-blind, active-controlled (moxifloxacin 400 mg single dose), multicenter QT study in adults with schizophrenia and schizoaffective disorder, and in three placebo- and active-controlled 6-week, fixed-dose efficacy trials in adults with schizophrenia.

In the QT study (n = 141), the 8 mg dose of immediate-release oral paliperidone (n=50) showed a mean placebo-subtracted increase from baseline in QTcLD of 12.3 msec (90% CI: 8.9; 15.6) on day 8 at 1.5 hours post-dose. The mean steady-state peak plasma concentration for this 8 mg dose of paliperidone immediate-release was more than twice the exposure observed with the maximum recommended 12 mg dose of INVEGA (C ss = 113 ng/mL and 45 ng/mL, respectively, when administered with a standard breakfast). In this same study, a 4 mg dose of the immediate-release oral formulation of paliperidone, for which C ss = 35 ng/mL, showed an increased placebo-subtracted QTcLD of 6.8 msec (90% CI: 3.6; 10.1) on day 2 at 1.5 hours post-dose. None of the subjects had a change exceeding 60 msec or a QTcLD exceeding 500 msec at any time during this study.®maxmax

For the three fixed-dose efficacy studies in subjects with schizophrenia, electrocardiogram (ECG) measurements taken at various time points showed only one subject in the INVEGA 12 mg group had a change exceeding 60 msec at one time-point on Day 6 (increase of 62 msec). No subject receiving INVEGA had a QTcLD exceeding 500 msec at any time in any of these three studies.®®

5.5 Tardive Dyskinesia

A syndrome of potentially irreversible, involuntary, dyskinetic movements may develop in patients treated with antipsychotic drugs. Although the prevalence of the syndrome appears to be highest among the elderly, especially elderly women, it is impossible to predict which patients will develop the syndrome. Whether antipsychotic drug products differ in their potential to cause tardive dyskinesia is unknown.

The risk of developing tardive dyskinesia and the likelihood that it will become irreversible appear to increase as the duration of treatment and the total cumulative dose of antipsychotic drugs administered to the patient increase, but the syndrome can develop after relatively brief treatment periods at low doses, although this is uncommon.

There is no known treatment for established tardive dyskinesia, although the syndrome may remit, partially or completely, if antipsychotic treatment is withdrawn. Antipsychotic treatment itself may suppress (or partially suppress) the signs and symptoms of the syndrome and may thus mask the underlying process. The effect of symptomatic suppression on the long-term course of the syndrome is unknown.

Given these considerations, INVEGA should be prescribed in a manner that is most likely to minimize the occurrence of tardive dyskinesia. Chronic antipsychotic treatment should generally be reserved for patients who suffer from a chronic illness that is known to respond to antipsychotic drugs. In patients who do require chronic treatment, the smallest dose and the shortest duration of treatment producing a satisfactory clinical response should be sought. The need for continued treatment should be reassessed periodically.®

If signs and symptoms of tardive dyskinesia appear in a patient treated with INVEGA , drug discontinuation should be considered. However, some patients may require treatment with INVEGA despite the presence of the syndrome.®®

5.6 Metabolic Changes

Atypical antipsychotic drugs have been associated with metabolic changes that may increase cardiovascular/cerebrovascular risk. These metabolic changes include hyperglycemia, dyslipidemia, and body weight gain. While all of the drugs in the class have been shown to produce some metabolic changes, each drug has its own specific risk profile.

Hyperglycemia and Diabetes Mellitus

Hyperglycemia and diabetes mellitus, in some cases extreme and associated with ketoacidosis or hyperosmolar coma or death, have been reported in patients treated with all atypical antipsychotics. These cases were, for the most part, seen in post-marketing clinical use and epidemiologic studies, not in clinical trials, and there have been few reports of hyperglycemia or diabetes in trial subjects treated with INVEGA . Assessment of the relationship between atypical antipsychotic use and glucose abnormalities is complicated by the possibility of an increased background risk of diabetes mellitus in patients with schizophrenia and the increasing incidence of diabetes mellitus in the general population. Given these confounders, the relationship between atypical antipsychotic use and hyperglycemia-related adverse events is not completely understood. However, epidemiological studies suggest an increased risk of treatment-emergent hyperglycemia-related adverse events in patients treated with the atypical antipsychotics. Because INVEGA was not marketed at the time these studies were performed, it is not known if INVEGA is associated with this increased risk.®®®

Patients with an established diagnosis of diabetes mellitus who are started on atypical antipsychotics should be monitored regularly for worsening of glucose control. Patients with risk factors for diabetes mellitus (e.g., obesity, family history of diabetes) who are starting treatment with atypical antipsychotics should undergo fasting blood glucose testing at the beginning of treatment and periodically during treatment. Any patient treated with atypical antipsychotics should be monitored for symptoms of hyperglycemia including polydipsia, polyuria, polyphagia, and weakness. Patients who develop symptoms of hyperglycemia during treatment with atypical antipsychotics should undergo fasting blood glucose testing. In some cases, hyperglycemia has resolved when the atypical antipsychotic was discontinued; however, some patients required continuation of anti-diabetic treatment despite discontinuation of the suspect drug.

Pooled data from the three placebo-controlled, 6-week, fixed-dose studies in adult subjects with schizophrenia are presented in Table 1a.

Table 1a. Change in Fasting Glucose from Three Placebo-Controlled, 6-Week, Fixed-Dose Studies in Adult Subjects with Schizophrenia
 |  |  | INVEGA®
 | Placebo | 3 mg/day | 6 mg/day | 9 mg/day | 12 mg/day
 | Mean change from baseline (mg/dL)
 | n=322 | n=122 | n=212 | n=234 | n=218
Serum Glucose Change from baseline | 0.8 | -0.7 | 0.4 | 2.3 | 4.3
 | Proportion of Patients with Shifts
Serum Glucose Normal to High | 5.1% | 3.2% | 4.5% | 4.8% | 3.8%
(<100 mg/dL to ≥126 mg/dL) | (12/236) | (3/93) | (7/156) | (9/187) | (6/157)

In the uncontrolled, longer-term open-label extension studies, INVEGA was associated with a mean change in glucose of +3.3 mg/dL at Week 24 (n=570) and +4.6 mg/dL at Week 52 (n=314).®

Data from the placebo-controlled 6-week study in adolescent subjects (12–17 years of age) with schizophrenia are presented in Table 1b.

Table 1b. Change in Fasting Glucose from a Placebo-Controlled 6-Week Study in Adolescent Subjects (12–17 years of age) with Schizophrenia
 |  | INVEGA®
 | Placebo | 1.5 mg/day | 3 mg/day | 6 mg/day | 12 mg/day
 | Mean change from baseline (mg/dL)
 | n=41 | n=44 | n=11 | n=28 | n=32
Serum Glucose Change from baseline | 0.8 | -1.4 | -1.8 | -0.1 | 5.2
 | Proportion of Patients with Shifts
Serum Glucose Normal to High | 3% | 0% | 0% | 0% | 11%
(<100 mg/dL to ≥126 mg/dL) | (1/32) | (0/34) | (0/9) | (0/20) | (3/27)

Dyslipidemia

Undesirable alterations in lipids have been observed in patients treated with atypical antipsychotics.

Pooled data from the three placebo-controlled, 6-week, fixed-dose studies in adult subjects with schizophrenia are presented in Table 2a.

Table 2a. Change in Fasting Lipids from Three Placebo-Controlled, 6-Week, Fixed-Dose Studies in Adult Subjects with Schizophrenia
 |  | INVEGA®
 | Placebo | 3 mg/day | 6 mg/day | 9 mg/day | 12 mg/day
 | Mean change from baseline (mg/dL)
Cholesterol | n=331 | n=120 | n=216 | n=236 | n=231
Change from baseline | -6.3 | -4.4 | -2.4 | -5.3 | -4.0
LDL | n=322 | n=116 | n=210 | n=231 | n=225
Change from baseline | -3.2 | 0.5 | -0.8 | -3.9 | -2.0
HDL | n=331 | n=119 | n=216 | n=234 | n=230
Change from baseline | 0.3 | -0.4 | 0.5 | 0.8 | 1.2
Triglycerides | n=331 | n=120 | n=216 | n=236 | n=231
Change from baseline | -22.3 | -18.3 | -12.6 | -10.6 | -15.4
 | Proportion of Patients with Shifts
Cholesterol
Normal to High | 2.6% | 2.8% | 5.6% | 4.1% | 3.1%
(<200 mg/dL to ≥240 mg/dL) | (5/194) | (2/71) | (7/125) | (6/147) | (4/130)
LDL
Normal to High | 1.9% | 0.0% | 5.0% | 3.7% | 0.0%
(<100 mg/dL to ≥160 mg/dL) | (2/105) | (0/44) | (3/60) | (3/81) | (0/69)
HDL
Normal to Low | 22.0% | 16.3% | 29.1% | 23.4% | 20.0%
(≥40 mg/dL to <40 mg/dL) | (44/200) | (13/80) | (39/134) | (32/137) | (27/135)
Triglycerides
Normal to High | 5.3% | 11.0% | 8.8% | 8.7% | 4.3%
(<150 mg/dL to ≥200 mg/dL) | (11/208) | (9/82) | (12/136) | (13/150) | (6/139)

In the uncontrolled, longer-term open-label extension studies, INVEGA was associated with a mean change in (a) total cholesterol of -1.5 mg/dL at Week 24 (n=573) and -1.5 mg/dL at Week 52 (n=317), (b) triglycerides of -6.4 mg/dL at Week 24 (n=573) and -10.5 mg/dL at Week 52 (n=317); (c) LDL of -1.9 mg/dL at Week 24 (n=557) and -2.7 mg/dL at Week 52 (n=297); and (d) HDL of +2.2 mg/dL at Week 24 (n=568) and +3.6 mg/dL at Week 52 (n=302).®

Data from the placebo-controlled 6-week study in adolescent subjects (12–17 years of age) with schizophrenia are presented in Table 2b.

Table 2b. Change in Fasting Lipids from a Placebo-Controlled 6-Week Study in Adolescent Subjects (12–17 years of age) with Schizophrenia
 |  | INVEGA®
 | Placebo | 1.5 mg/day | 3 mg/day | 6 mg/day | 12 mg/day
 | Mean change from baseline (mg/dL)
Cholesterol | n=39 | n=45 | n=11 | n=28 | n=32
Change from baseline | -7.8 | -3.3 | 12.7 | 3.0 | -1.5
LDL | n=37 | n=40 | n=9 | n=27 | n=31
Change from baseline | -4.1 | -3.1 | 7.2 | 2.4 | 0.6
HDL | n=37 | n=41 | n=9 | n=27 | n=31
Change from baseline | -1.9 | 0.0 | 1.3 | 1.4 | 0.0
Triglycerides | n=39 | n=44 | n=11 | n=28 | n=32
Change from baseline | -8.9 | 3.2 | 17.6 | -5.4 | 3.9
 | Proportion of Patients with Shifts
Cholesterol
Normal to High | 7% | 4% | 0% | 6% | 11%
(<170 mg/dL to ≥200 mg/dL) | (2/27) | (1/26) | (0/6) | (1/18) | (2/19)
LDL
Normal to High | 3% | 4% | 14% | 0% | 9%
(<110 mg/dL to ≥130 mg/dL) | (1/32) | (1/25) | (1/7) | (0/22) | (2/22)
HDL
Normal to Low | 14% | 7% | 29% | 13% | 23%
(≥40 mg/dL to <40 mg/dL) | (4/28) | (2/30) | (2/7) | (3/23) | (5/22)
Triglycerides
Normal to High | 3% | 5% | 13% | 8% | 7%
(<150 mg/dL to ≥200 mg/dL) | (1/34) | (2/38) | (1/8) | (2/26) | (2/28)

Weight Gain

Weight gain has been observed with atypical antipsychotic use. Clinical monitoring of weight is recommended.

Schizophrenia Trials

Data on mean changes in body weight and the proportion of subjects meeting a weight gain criterion of ≥ 7% of body weight from the three placebo-controlled, 6-week, fixed-dose studies in adult subjects are presented in Table 3a.

Table 3a. Mean Change in Body Weight (kg) and the Proportion of Subjects with ≥ 7% Gain in Body Weight from Three Placebo-Controlled, 6-Week, Fixed-Dose Studies in Adult Subjects with Schizophrenia
 |  | INVEGA®
 | Placebo | 3 mg/day | 6 mg/day | 9 mg/day | 12 mg/day
 | n=323 | n=112 | n=215 | n=235 | n=218
Weight (kg) Change from baseline | -0.4 | 0.6 | 0.6 | 1.0 | 1.1
Weight Gain ≥ 7% increase from baseline | 5% | 7% | 6% | 9% | 9%

In the uncontrolled, longer-term open-label extension studies, INVEGA was associated with a mean change in weight of +1.4 kg at Week 24 (n=63) and +2.6 kg at Week 52 (n=302).®

Weight gain in adolescent subjects with schizophrenia was assessed in a 6-week, double-blind, placebo-controlled study and an open-label extension with a median duration of exposure to INVEGA of 182 days. Data on mean changes in body weight and the proportion of subjects meeting a weight gain criterion of ≥ 7% of body weight from the placebo-controlled 6-week study in adolescent subjects (12–17 years of age) are presented in Table 3b.® [see ] Clinical Studies (14.1)

Table 3b. Mean Change in Body Weight (kg) and the Proportion of Subjects with ≥ 7% Gain in Body Weight from a Placebo-Controlled 6-Week Study in Adolescent Subjects (12–17 years of age) with Schizophrenia
 |  | INVEGA®
 | Placebo | 1.5 mg/day | 3 mg/day | 6 mg/day | 12 mg/day
 | n=51 | n=54 | n=16 | n=45 | n=34
Weight (kg) Change from baseline | 0.0 | 0.3 | 0.8 | 1.2 | 1.5
Weight Gain ≥ 7% increase from baseline | 2% | 6% | 19% | 7% | 18%

In the open-label long-term study the proportion of total subjects treated with INVEGA with an increase in body weight of ≥ 7% from baseline was 33%. When treating adolescent patients with INVEGA , weight gain should be assessed against that expected with normal growth. When taking into consideration the median duration of exposure to INVEGA in the open-label study (182 days) along with expected normal growth in this population based on age and gender, an assessment of standardized scores relative to normative data provides a more clinically relevant measure of changes in weight. The mean change from open-label baseline to endpoint in standardized score for weight was 0.1 (4% above the median for normative data). Based on comparison to the normative data, these changes are not considered to be clinically significant.®®®

Schizoaffective Disorder Trials

In the pooled data from the two placebo-controlled, 6-week studies in adult subjects with schizoaffective disorder, a higher percentage of INVEGA -treated subjects (5%) had an increase in body weight of ≥ 7% compared with placebo-treated subjects (1%). In the study that examined high- and low-dose groups, the increase in body weight of ≥ 7% was 3% in the low-dose group, 7% in the high-dose group, and 1% in the placebo group.®

5.7 Hyperprolactinemia

Like other drugs that antagonize dopamine D receptors, paliperidone elevates prolactin levels and the elevation persists during chronic administration. Paliperidone has a prolactin-elevating effect similar to that seen with risperidone, a drug that is associated with higher levels of prolactin than other antipsychotic drugs.2

Hyperprolactinemia, regardless of etiology, may suppress hypothalamic GnRH, resulting in reduced pituitary gonadotrophin secretion. This, in turn, may inhibit reproductive function by impairing gonadal steroidogenesis in both female and male patients. Galactorrhea, amenorrhea, gynecomastia, and impotence have been reported in patients receiving prolactin-elevating compounds. Long-standing hyperprolactinemia when associated with hypogonadism may lead to decreased bone density in both female and male subjects.

Tissue culture experiments indicate that approximately one-third of human breast cancers are prolactin dependent , a factor of potential importance if the prescription of these drugs is considered in a patient with previously detected breast cancer. An increase in the incidence of pituitary gland, mammary gland, and pancreatic islet cell neoplasia (mammary adenocarcinomas, pituitary and pancreatic adenomas) was observed in the risperidone carcinogenicity studies conducted in mice and rats . Neither clinical studies nor epidemiologic studies conducted to date have shown an association between chronic administration of this class of drugs and tumorigenesis in humans, but the available evidence is too limited to be conclusive. in vitro [see ] Nonclinical Toxicology (13.1)

5.8 Potential for Gastrointestinal Obstruction

Because the INVEGA tablet is non-deformable and does not appreciably change in shape in the gastrointestinal tract, INVEGA should ordinarily not be administered to patients with pre-existing severe gastrointestinal narrowing (pathologic or iatrogenic, for example: esophageal motility disorders, small bowel inflammatory disease, "short gut" syndrome due to adhesions or decreased transit time, past history of peritonitis, cystic fibrosis, chronic intestinal pseudoobstruction, or Meckel's diverticulum). There have been rare reports of obstructive symptoms in patients with known strictures in association with the ingestion of drugs in non-deformable controlled-release formulations. Because of the controlled-release design of the tablet, INVEGA should only be used in patients who are able to swallow the tablet whole .®®® [see and ] Dosage and Administration (2.3) Patient Counseling Information (17.8)

A decrease in transit time, e.g., as seen with diarrhea, would be expected to decrease bioavailability and an increase in transit time, e.g., as seen with gastrointestinal neuropathy, diabetic gastroparesis, or other causes, would be expected to increase bioavailability. These changes in bioavailability are more likely when the changes in transit time occur in the upper GI tract.

5.9 Orthostatic Hypotension and Syncope

Paliperidone can induce orthostatic hypotension and syncope in some patients because of its alpha-blocking activity. In pooled results of the three placebo-controlled, 6-week, fixed-dose trials in subjects with schizophrenia, syncope was reported in 0.8% (7/850) of subjects treated with INVEGA (3 mg, 6 mg, 9 mg, 12 mg) compared to 0.3% (1/355) of subjects treated with placebo. INVEGA should be used with caution in patients with known cardiovascular disease (e.g., heart failure, history of myocardial infarction or ischemia, conduction abnormalities), cerebrovascular disease, or conditions that predispose the patient to hypotension (e.g., dehydration, hypovolemia, and treatment with antihypertensive medications). Monitoring of orthostatic vital signs should be considered in patients who are vulnerable to hypotension.®®

5.10 Leukopenia, Neutropenia, and Agranulocytosis

In clinical trial and/or postmarketing experience, events of leukopenia/neutropenia have been reported temporally related to antipsychotic agents, including INVEGA . Agranulocytosis has also been reported. Class Effect:®

Possible risk factors for leukopenia/neutropenia include pre-existing low white blood cell count (WBC) and history of drug-induced leukopenia/neutropenia. Patients with a history of a clinically significant low WBC or a drug-induced leukopenia/neutropenia should have their complete blood count (CBC) monitored frequently during the first few months of therapy and discontinuation of INVEGA should be considered at the first sign of a clinically significant decline in WBC in the absence of other causative factors.®

Patients with clinically significant neutropenia should be carefully monitored for fever or other symptoms or signs of infection and treated promptly if such symptoms or signs occur. Patients with severe neutropenia (absolute neutrophil count <1000/mm) should discontinue INVEGA and have their WBC followed until recovery.^3®

5.11 Potential for Cognitive and Motor Impairment

Somnolence was reported in subjects treated with INVEGA . Antipsychotics, including INVEGA , have the potential to impair judgment, thinking, or motor skills. Patients should be cautioned about performing activities requiring mental alertness, such as operating hazardous machinery or operating a motor vehicle, until they are reasonably certain that paliperidone therapy does not adversely affect them.® [see ,)] Adverse Reactions (6.16.2®

5.12 Seizures

During premarketing clinical trials in subjects with schizophrenia (the three placebo-controlled, 6-week, fixed-dose studies and a study conducted in elderly schizophrenic subjects), seizures occurred in 0.22% of subjects treated with INVEGA (3 mg, 6 mg, 9 mg, 12 mg) and 0.25% of subjects treated with placebo. Like other antipsychotic drugs, INVEGA should be used cautiously in patients with a history of seizures or other conditions that potentially lower the seizure threshold. Conditions that lower the seizure threshold may be more prevalent in patients 65 years or older.®®

5.13 Dysphagia

Esophageal dysmotility and aspiration have been associated with antipsychotic drug use. Aspiration pneumonia is a common cause of morbidity and mortality in patients with advanced Alzheimer's dementia. INVEGA and other antipsychotic drugs should be used cautiously in patients at risk for aspiration pneumonia.®

5.14 Suicide

The possibility of suicide attempt is inherent in psychotic illnesses, and close supervision of high-risk patients should accompany drug therapy. Prescriptions for INVEGA should be written for the smallest quantity of tablets consistent with good patient management in order to reduce the risk of overdose.®

5.15 Priapism

Drugs with alpha-adrenergic blocking effects have been reported to induce priapism. Priapism has been reported with INVEGA during postmarketing surveillance. Severe priapism may require surgical intervention.®

5.16 Thrombotic Thrombocytopenic Purpura (TTP)

No cases of TTP were observed during clinical studies with paliperidone. Although cases of TTP have been reported in association with risperidone administration, the relationship to risperidone therapy is unknown.

5.17 Body Temperature Regulation

Disruption of the body's ability to reduce core body temperature has been attributed to antipsychotic agents. Appropriate care is advised when prescribing INVEGA to patients who will be experiencing conditions which may contribute to an elevation in core body temperature, e.g., exercising strenuously, exposure to extreme heat, receiving concomitant medication with anticholinergic activity, or being subject to dehydration.®

5.18 Antiemetic Effect

An antiemetic effect was observed in preclinical studies with paliperidone. This effect, if it occurs in humans, may mask the signs and symptoms of overdosage with certain drugs or of conditions such as intestinal obstruction, Reye's syndrome, and brain tumor.

5.19 Use in Patients with Concomitant Illness

Clinical experience with INVEGA in patients with certain concomitant illnesses is limited .® [see ] Clinical Pharmacology (12.3)

Patients with Parkinson's Disease or Dementia with Lewy Bodies are reported to have an increased sensitivity to antipsychotic medication. Manifestations of this increased sensitivity include confusion, obtundation, postural instability with frequent falls, extrapyramidal symptoms, and clinical features consistent with the neuroleptic malignant syndrome.

INVEGA has not been evaluated or used to any appreciable extent in patients with a recent history of myocardial infarction or unstable heart disease. Patients with these diagnoses were excluded from premarketing clinical trials. Because of the risk of orthostatic hypotension with INVEGA , caution should be observed in patients with known cardiovascular disease .®® [see ] Warnings and Precautions (5.9)

5.20 Monitoring: Laboratory Tests

No specific laboratory tests are recommended.

6 ADVERSE REACTIONS

6.1 Overall Adverse Reaction Profile

The following adverse reactions are discussed in more detail in other sections of the labeling:

- Increased mortality in elderly patients with dementia-related psychosis [see and ] Boxed Warning Warnings and Precautions (5.1)
- Cerebrovascular adverse reactions, including stroke, in elderly patients with dementia-related psychosis [see ] Warnings and Precautions (5.2)
- Neuroleptic malignant syndrome [see ] Warnings and Precautions (5.3)
- QT prolongation [see ] Warnings and Precautions (5.4)
- Tardive dyskinesia [see ] Warnings and Precautions (5.5)
- Metabolic changes [see ] Warnings and Precautions (5.6)
- Hyperprolactinemia [see ] Warnings and Precautions (5.7)
- Potential for gastrointestinal obstruction [see ] Warnings and Precautions (5.8)
- Orthostatic hypotension and syncope [see ] Warnings and Precautions (5.9)
- Leukopenia, neutropenia, and agranulocytosis [see ] Warnings and Precautions (5.10)
- Potential for cognitive and motor impairment [see ] Warnings and Precautions (5.11)
- Seizures [see ] Warnings and Precautions (5.12)
- Dysphagia [see ] Warnings and Precautions (5.13)
- Suicide [see ] Warnings and Precautions (5.14)
- Priapism [see ] Warnings and Precautions (5.15)
- Thrombotic thrombocytopenic purpura (TTP) [see ] Warnings and Precautions (5.16)
- Disruption of body temperature regulation [see ] Warnings and Precautions (5.17)
- Antiemetic effect [see ] Warnings and Precautions (5.18)
- Increased sensitivity in patients with Parkinson's disease or those with dementia with Lewy bodies [see ] Warnings and Precautions (5.19)
- Diseases or conditions that could affect metabolism or hemodynamic responses [see ] Warnings and Precautions (5.19)

The most common adverse reactions in clinical trials in adult subjects with schizophrenia (reported in 5% or more of subjects treated with INVEGA and at least twice the placebo rate in any of the dose groups) were extrapyramidal symptoms, tachycardia, and akathisia. The most common adverse reactions in clinical trials in adult patients with schizoaffective disorder (reported in 5% or more of subjects treated with INVEGA and at least twice the placebo rate) were extrapyramidal symptoms, somnolence, dyspepsia, constipation, weight increased, and nasopharyngitis.®®

The most common adverse reactions that were associated with discontinuation from clinical trials in adult subjects with schizophrenia (causing discontinuation in 2% of INVEGA -treated subjects) were nervous system disorders. The most common adverse reactions that were associated with discontinuation from clinical trials in adult subjects with schizoaffective disorder were gastrointestinal disorders, which resulted in discontinuation in 1% of INVEGA -treated subjects. .®® [See ] Adverse Reactions (6.4)

The safety of INVEGA was evaluated in 1205 adult subjects with schizophrenia who participated in three placebo-controlled, 6-week, double-blind trials, of whom 850 subjects received INVEGA at fixed doses ranging from 3 mg to 12 mg once daily. The information presented in this section was derived from pooled data from these three trials. Additional safety information from the placebo-controlled phase of the long-term maintenance study, in which subjects received INVEGA at daily doses within the range of 3 mg to 15 mg (n=104), is also included.®®®

The safety of INVEGA was evaluated in 150 adolescent subjects 12–17 years of age with schizophrenia who received INVEGA in the dose range of 1.5 mg to 12 mg/day in a 6-week, double-blind, placebo-controlled trial.®®

The safety of INVEGA was also evaluated in 622 adult subjects with schizoaffective disorder who participated in two placebo-controlled, 6-week, double-blind trials. In one of these trials, 206 subjects were assigned to one of two dose levels of INVEGA : 6 mg with the option to reduce to 3 mg (n = 108) or 12 mg with the option to reduce to 9 mg (n = 98) once daily. In the other study, 214 subjects received flexible doses of INVEGA (3–12 mg once daily). Both studies included subjects who received INVEGA either as monotherapy or as an adjunct to mood stabilizers and/or antidepressants. Adverse events during exposure to study treatment were obtained by general inquiry and recorded by clinical investigators using their own terminology. Consequently, to provide a meaningful estimate of the proportion of individuals experiencing adverse events, events were grouped in standardized categories using MedDRA terminology.®®®®

Throughout this section, adverse reactions are reported. Adverse reactions are adverse events that were considered to be reasonably associated with the use of INVEGA (adverse drug reactions) based on the comprehensive assessment of the available adverse event information. A causal association for INVEGA often cannot be reliably established in individual cases. Further, because clinical trials are conducted under widely varying conditions, adverse reaction rates observed in the clinical trials of a drug cannot be directly compared to rates in the clinical trials of another drug and may not reflect the rates observed in clinical practice.®®

6.2 Commonly-Observed Adverse Reactions in Double-Blind, Placebo-Controlled Clinical Trials – Schizophrenia in Adults and Adolescents

Adult Patients with Schizophrenia

enumerates the pooled incidences of adverse reactions reported in the three placebo-controlled, 6-week, fixed-dose studies in adults, listing those that occurred in 2% or more of subjects treated with INVEGA in any of the dose groups, and for which the incidence in INVEGA -treated subjects in any of the dose groups was greater than the incidence in subjects treated with placebo. Table 4®®

Table 4. Adverse Reactions Reported by ≥ 2% of INVEGA -Treated Adult Subjects with Schizophrenia in Three Short-Term, Fixed-Dose, Placebo-Controlled Clinical Trials® [Table includes adverse reactions that were reported in 2% or more of subjects in any of the INVEGA dose groups and which occurred at greater incidence than in the placebo group. Data are pooled from three studies; one study included once-daily INVEGA doses of 3 mg and 9 mg, the second study included 6 mg, 9 mg, and 12 mg, and the third study included 6 mg and 12 mg . Extrapyramidal symptoms includes the terms dyskinesia, dystonia, extrapyramidal disorder, hypertonia, muscle rigidity, oculogyration, parkinsonism, and tremor. Somnolence includes the terms sedation and somnolence. Tachycardia includes the terms tachycardia, sinus tachycardia, and heart rate increased. Adverse reactions for which the INVEGA incidence was equal to or less than placebo are not listed in the table, but included the following: vomiting.®® [see ] Clinical Studies (14)®]
 | Percentage of Patients
 |  | INVEGA®
 | Placebo | 3 mg once daily | 6 mg once daily | 9 mg once daily | 12 mg once daily
Body System or Organ Class | (N=355) | (N=127) | (N=235) | (N=246) | (N=242)
Dictionary-Derived Term
Total percentage of subjects with adverse reactions | 37 | 48 | 47 | 53 | 59
Cardiac disorders
Atrioventricular block first degree | 1 | 2 | 0 | 2 | 1
Bundle branch block | 2 | 3 | 1 | 3 | <1
Sinus arrhythmia | 0 | 2 | 1 | 1 | <1
Tachycardia | 7 | 14 | 12 | 12 | 14
Gastrointestinal disorders
Abdominal pain upper | 1 | 1 | 3 | 2 | 2
Dry mouth | 1 | 2 | 3 | 1 | 3
Salivary hypersecretion | <1 | 0 | <1 | 1 | 4
General disorders
Asthenia | 1 | 2 | <1 | 2 | 2
Fatigue | 1 | 2 | 1 | 2 | 2
Nervous system disorders
Akathisia | 4 | 4 | 3 | 8 | 10
Dizziness | 4 | 6 | 5 | 4 | 5
Extrapyramidal symptoms | 8 | 10 | 7 | 20 | 18
Headache | 12 | 11 | 12 | 14 | 14
Somnolence | 7 | 6 | 9 | 10 | 11
Vascular disorders
Orthostatic hypotension | 1 | 2 | 1 | 2 | 4

Adolescent Patients with Schizophrenia

lists the adverse reactions reported in a fixed-dose, placebo-controlled study in adolescent subjects 12–17 years of age with schizophrenia, listing those that occurred in 2% or more of subjects treated with INVEGA in any of the dose groups, and for which the incidence in INVEGA -treated subjects in any of the dose groups was greater than the incidence in subjects treated with placebo. Table 5®®

Table 5. Adverse Reactions Reported by ≥ 2% of INVEGA -Treated Adolescent Subjects with Schizophrenia in a Fixed-Dose, Placebo-Controlled Clinical Trial® [Table includes adverse reactions that were reported in 2% or more of subjects in any of the INVEGA dose groups and which occurred at greater incidence than in the placebo group. Extrapyramidal symptoms includes the terms oculogyric crisis, muscle rigidity, musculoskeletal stiffness, nuchal rigidity, torticollis, trismus, bradykinesia, cogwheel rigidity, dyskinesia, dystonia, extrapyramidal disorder, hypertonia, hypokinesia, muscle contractions involuntary, parkinsonian gait, parkinsonism, tremor, and restlessness. Somnolence includes the terms somnolence, sedation, and hypersomnia. Insomnia includes the terms insomnia and initial insomnia. Tachycardia includes the terms tachycardia, sinus tachycardia, and heart rate increased. Hypertension includes the terms hypertension and blood pressure increased. Gynecomastia includes the terms gynecomastia and breast swelling.®]
 | Percentage of Patients
 |  | INVEGA®
 | Placebo | 1.5 mg once daily | 3 mg once daily | 6 mg once daily | 12 mg once daily
Body System or Organ Class | (N=51) | (N=54) | (N=16) | (N=45) | (N=35)
Dictionary-Derived Term
Total percentage of subjects with adverse reactions | 43 | 37 | 50 | 58 | 74
Cardiac disorders
Tachycardia | 0 | 0 | 6 | 9 | 6
Eye disorders
Vision blurred | 0 | 0 | 0 | 0 | 3
Gastrointestinal disorders
Dry mouth | 2 | 0 | 0 | 0 | 3
Salivary hypersecretion | 0 | 2 | 6 | 2 | 0
Swollen tongue | 0 | 0 | 0 | 0 | 3
Vomiting | 10 | 0 | 6 | 11 | 3
General disorders
Asthenia | 0 | 0 | 0 | 2 | 3
Fatigue | 0 | 4 | 0 | 2 | 3
Infections and infestations
Nasopharyngitis | 2 | 4 | 0 | 4 | 0
Investigations
Weight increased | 0 | 7 | 6 | 2 | 3
Nervous system disorders
Akathisia | 0 | 4 | 6 | 11 | 17
Dizziness | 0 | 2 | 6 | 2 | 3
Extrapyramidal symptoms | 0 | 4 | 19 | 18 | 23
Headache | 4 | 9 | 6 | 4 | 14
Lethargy | 0 | 0 | 0 | 0 | 3
Somnolence | 4 | 9 | 13 | 20 | 26
Tongue paralysis | 0 | 0 | 0 | 0 | 3
Psychiatric disorders
Anxiety | 4 | 0 | 0 | 2 | 9
Reproductive system and breast disorders
Amenorrhea | 0 | 0 | 6 | 0 | 0
Galactorrhea | 0 | 0 | 0 | 4 | 0
Gynecomastia | 0 | 0 | 0 | 0 | 3
Respiratory, thoracic and mediastinal disorders
Epistaxis | 0 | 0 | 0 | 2 | 0

6.3 Commonly-Observed Adverse Reactions in Double-Blind, Placebo-Controlled Clinical Trials – Schizoaffective Disorder in Adults

enumerates the pooled incidences of adverse reactions reported in the two placebo-controlled 6-week studies in adult subjects, listing those that occurred in 2% or more of subjects treated with INVEGA and for which the incidence in INVEGA -treated subjects was greater than the incidence in subjects treated with placebo. Table 6®®

Table 6. Adverse Drug Reactions Reported by ≥ 2% of INVEGA -Treated Adult Subjects with Schizoaffective Disorder in Two Double-Blind, Placebo-Controlled Clinical Trials® [Table includes adverse reactions that were reported in 2% or more of subjects in any of the INVEGA dose groups and which occurred at greater incidence than in the placebo group. Data are pooled from two studies. One study included once-daily INVEGA doses of 6 mg (with the option to reduce to 3 mg) and 12 mg (with the option to reduce to 9 mg). The second study included flexible once-daily doses of 3 to 12 mg. Among the 420 subjects treated with INVEGA , 230 (55%) received INVEGA as monotherapy and 190 (45%) received INVEGA as an adjunct to mood stabilizers and/or antidepressants. Extrapyramidal symptoms includes the terms bradykinesia, drooling, dyskinesia, dystonia, hypertonia, muscle rigidity, muscle twitching, oculogyration, parkinsonian gait, parkinsonism, restlessness, and tremor. Somnolence includes the terms sedation and somnolence. Tachycardia includes the terms tachycardia, sinus tachycardia, and heart rate increased.®®®®®]
 | Percentage of Patients
 |  | INVEGA® | INVEGA® | INVEGA®
 | Placebo | 3–6 mg once-daily fixed-dose range | 9–12 mg once-daily fixed-dose range | 3–12 mg once-daily flexible dose
Body System or Organ Class | (N=202) | (N=108) | (N=98) | (N=214)
Dictionary-Derived Term
Total percentage of subjects with adverse reactions | 32 | 48 | 50 | 43
Cardiac disorders
Tachycardia | 2 | 3 | 1 | 2
Gastrointestinal disorders
Abdominal discomfort/Abdominal pain upper | 1 | 1 | 0 | 3
Constipation | 2 | 4 | 5 | 4
Dyspepsia | 2 | 5 | 6 | 6
Nausea | 6 | 8 | 8 | 5
Stomach discomfort | 1 | 0 | 1 | 2
General disorders
Asthenia | 1 | 3 | 4 | <1
Infections and Infestations
Nasopharyngitis | 1 | 2 | 5 | 3
Rhinitis | 0 | 1 | 3 | 1
Upper respiratory tract infection | 1 | 2 | 2 | 2
Investigations
Weight increased | 1 | 5 | 4 | 4
Metabolism and nutrition disorders
Decreased appetite | <1 | 1 | 0 | 2
Increased appetite | <1 | 3 | 2 | 2
Musculoskeletal and connective tissue disorders
Back pain | 1 | 1 | 1 | 3
Myalgia | <1 | 2 | 4 | 1
Nervous system disorders
Akathisia | 4 | 4 | 6 | 6
Dysarthria | 0 | 1 | 4 | 2
Extrapyramidal symptoms | 8 | 20 | 17 | 12
Somnolence | 5 | 12 | 12 | 8
Psychiatric disorders
Sleep disorder | <1 | 2 | 3 | 0
Respiratory, thoracic and mediastinal disorders
Cough | 1 | 1 | 3 | 1
Pharyngolaryngeal pain | <1 | 0 | 2 | 1

Monotherapy versus Adjunctive Therapy

The designs of the two placebo-controlled, 6-week, double-blind trials in adult subjects with schizoaffective disorder included the option for subjects to receive antidepressants (except monoamine oxidase inhibitors) and/or mood stabilizers (lithium, valproate, or lamotrigine). In the subject population evaluated for safety, 230 (55%) subjects received INVEGA as monotherapy and 190 (45%) subjects received INVEGA as an adjunct to mood stabilizers and/or antidepressants. When comparing these 2 subpopulations, only nausea occurred at a greater frequency (≥ 3% difference) in subjects receiving INVEGA as monotherapy.®®®

6.4 Discontinuations Due to Adverse Reactions

Schizophrenia Trials

The percentages of subjects who discontinued due to adverse reactions in the three schizophrenia placebo-controlled, 6-week, fixed-dose studies in adults were 3% and 1% in INVEGA - and placebo-treated subjects, respectively. The most common reasons for discontinuation were nervous system disorders (2% and 0% in INVEGA - and placebo-treated subjects, respectively).®®

Among the adverse reactions in the 6-week, fixed-dose, placebo-controlled study in adolescents with schizophrenia, only dystonia led to discontinuation (<1% of INVEGA -treated subjects).®

Schizoaffective Disorder Trials

The percentages of subjects who discontinued due to adverse reactions in the two schizoaffective disorder placebo-controlled 6-week studies in adults were 1% and <1% in INVEGA - and placebo-treated subjects, respectively. The most common reasons for discontinuation were gastrointestinal disorders (1% and 0% in INVEGA - and placebo-treated subjects, respectively).®®

6.5 Dose-Related Adverse Reactions

Schizophrenia Trials

Based on the pooled data from the three placebo-controlled, 6-week, fixed-dose studies in adult subjects with schizophrenia, among the adverse reactions that occurred with a greater than 2% incidence in the subjects treated with INVEGA , the incidences of the following adverse reactions increased with dose: somnolence, orthostatic hypotension, akathisia, dystonia, extrapyramidal disorder, hypertonia, parkinsonism, and salivary hypersecretion. For most of these, the increased incidence was seen primarily at the 12 mg dose, and, in some cases, the 9 mg dose.®

In the 6-week, fixed-dose, placebo-controlled study in adolescents with schizophrenia, among the adverse reactions that occurred with >2% incidence in the subjects treated with INVEGA , the incidences of the following adverse reactions increased with dose: tachycardia, akathisia, extrapyramidal symptoms, somnolence, and headache.®

Schizoaffective Disorder Trials

In a placebo-controlled, 6-week, high- and low-dose study in adult subjects with schizoaffective disorder, akathisia, dystonia, dysarthria, myalgia, nasopharyngitis, rhinitis, cough, and pharyngolaryngeal pain occurred more frequently (i.e., a difference of at least 2%) in subjects who received higher doses of INVEGA compared with subjects who received lower doses.®

6.6 Demographic Differences

An examination of population subgroups in the three placebo-controlled, 6-week, fixed-dose studies in adult subjects with schizophrenia and in the two placebo-controlled, 6-week studies in adult subjects with schizoaffective disorder did not reveal any evidence of clinically relevant differences in safety on the basis of gender or race alone; there was also no difference on the basis of age . [see ] Use in Specific Populations (8.5)

6.7 Extrapyramidal Symptoms (EPS)

Pooled data from the three placebo-controlled, 6-week, fixed-dose studies in adult subjects with schizophrenia provided information regarding treatment-emergent EPS. Several methods were used to measure EPS: (1) the Simpson-Angus global score (mean change from baseline) which broadly evaluates Parkinsonism, (2) the Barnes Akathisia Rating Scale global clinical rating score (mean change from baseline) which evaluates akathisia, (3) use of anticholinergic medications to treat emergent EPS (), and (4) incidence of spontaneous reports of EPS (). For the Simpson-Angus Scale, spontaneous EPS reports and use of anticholinergic medications, there was a dose-related increase observed for the 9 mg and 12 mg doses. There was no difference observed between placebo and INVEGA 3 mg and 6 mg doses for any of these EPS measures. Table 7 Table 8®

Table 7. Treatment-Emergent Extrapyramidal Symptoms (EPS) Assessed by Incidence of Ratings Scales and Use of Anticholinergic Medication – Schizophrenia Studies in Adults
 | Percentage of Patients
 |  | INVEGA®
 | Placebo | 3 mg once daily | 6 mg once daily | 9 mg once daily | 12 mg once daily
EPS Group | (N=355) | (N=127) | (N=235) | (N=246) | (N=242)
Parkinsonism [For Parkinsonism, percent of patients with Simpson-Angus global score > 0.3 (Global score defined as total sum of items score divided by the number of items)] | 9 | 11 | 3 | 15 | 14
Akathisia [For Akathisia, percent of patients with Barnes Akathisia Rating Scale global score ≥ 2] | 6 | 6 | 4 | 7 | 9
Use of anticholinergic medications [Percent of patients who received anticholinergic medications to treat emergent EPS] | 10 | 10 | 9 | 22 | 22

Table 8. Treatment-Emergent Extrapyramidal Symptoms (EPS)-Related Adverse Events by MedDRA Preferred Term – Schizophrenia Studies in Adults
 | Percentage of Patients
 |  | INVEGA®
 | Placebo | 3 mg once daily | 6 mg once daily | 9 mg once daily | 12 mg once daily
EPS Group | (N=355) | (N=127) | (N=235) | (N=246) | (N=242)
Overall percentage of patients with EPS-related AE | 11 | 13 | 10 | 25 | 26
Dyskinesia | 3 | 5 | 3 | 8 | 9
Dystonia | 1 | 1 | 1 | 5 | 5
Hyperkinesia | 4 | 4 | 3 | 8 | 10
Parkinsonism | 2 | 3 | 3 | 7 | 6
Tremor | 3 | 3 | 3 | 4 | 3
Dyskinesia group includes: Dyskinesia, extrapyramidal disorder, muscle twitching, tardive dyskinesia
Dystonia group includes: Dystonia, muscle spasms, oculogyration, trismus
Hyperkinesia group includes: Akathisia, hyperkinesia
Parkinsonism group includes: Bradykinesia, cogwheel rigidity, drooling, hypertonia, hypokinesia, muscle rigidity, musculoskeletal stiffness, parkinsonism
Tremor group includes: Tremor

Compared to data from the studies in adults subjects with schizophrenia, pooled data from the two placebo-controlled 6-week studies in adult subjects with schizoaffective disorder showed similar types and frequencies of EPS as measured by rating scales, anticholinergic medication use, and spontaneous reports of EPS-related adverse events. For subjects with schizoaffective disorder, there was no dose-related increase in EPS observed for parkinsonism with the Simpson-Angus scale or akathisia with the Barnes Akathisia Rating Scale. There was a dose-related increase observed with spontaneous EPS reports of hyperkinesia and dystonia and in the use of anticholinergic medications.

shows the EPS data from the pooled schizoaffective disorder trials. Table 9

Table 9. Treatment-Emergent Extrapyramidal Symptoms (EPS)-Related Adverse Events by MedDRA Preferred Term – Schizoaffective Disorder Studies in Adults
 | Percentage of Patients
 |  | INVEGA®
 | Placebo | 3–6 mg once-daily fixed-dose range | 9–12 mg once-daily fixed-dose range | 3–12 mg once-daily flexible dose
EPS Group | (N=202) | (N=108) | (N=98) | (N=214)
Overall percentage of patients with EPS-related AE | 11 | 23 | 22 | 17
Dyskinesia | 1 | 3 | 1 | 1
Dystonia | 1 | 2 | 3 | 2
Hyperkinesia | 5 | 5 | 8 | 7
Parkinsonism | 3 | 14 | 7 | 7
Tremor | 3 | 12 | 11 | 5
Dyskinesia group includes: Dyskinesia, muscle twitching
Dystonia group includes: Dystonia, muscle spasms, oculogyration
Hyperkinesia group includes: Akathisia, hyperkinesia, restlessness
Parkinsonism group includes: Bradykinesia, drooling, hypertonia, muscle rigidity, muscle tightness, musculoskeletal stiffness, parkinsonian gait, parkinsonism
Tremor group includes: Tremor

The incidences of EPS-related adverse events in the adolescent schizophrenia studies showed a similar dose-related pattern to those in the adult studies. There were notably higher incidences of dystonia, hyperkinesia, tremor, and parkinsonism in the adolescent population as compared to the adult studies . (Table 10)

Table 10. Treatment-Emergent Extrapyramidal Symptoms (EPS)-Related Adverse Events by MedDRA Preferred Term – Schizophrenia Studies in Adolescent Subjects
 | Percentage of Patients
 |  | INVEGA®
 | Placebo | 1.5 mg once daily | 3 mg once daily | 6 mg once daily | 12 mg once daily
EPS Group | (N=51) | (N=54) | (N=16) | (N=45) | (N=35)
Overall percentage of patients with EPS-related AE | 0 | 6 | 25 | 22 | 40
Hyperkinesia | 0 | 4 | 6 | 11 | 17
Dystonia | 0 | 2 | 0 | 11 | 14
Tremor | 0 | 2 | 6 | 7 | 11
Parkinsonism | 0 | 0 | 6 | 2 | 14
Dyskinesia | 0 | 2 | 6 | 2 | 6
Hyperkinesia group includes: Akathisia
Dystonia group includes: Dystonia, muscle contracture, oculogyric crisis, tongue paralysis, torticollis
Tremor group includes: Tremor
Parkinsonism group includes: Cogwheel rigidity, extrapyramidal disorder, muscle rigidity
Dyskinesia group includes: Dyskinesia, muscle contractions involuntary

Dystonia

Symptoms of dystonia, prolonged abnormal contractions of muscle groups, may occur in susceptible individuals during the first few days of treatment. Dystonic symptoms include: spasm of the neck muscles, sometimes progressing to tightness of the throat, swallowing difficulty, difficulty breathing, and/or protrusion of the tongue. While these symptoms can occur at low doses, they occur more frequently and with greater severity with high potency and at higher doses of first generation antipsychotic drugs. An elevated risk of acute dystonia is observed in males and younger age groups. Class Effect:

6.8 Laboratory Test Abnormalities

In the pooled data from the three placebo-controlled, 6-week, fixed-dose studies in adult subjects with schizophrenia and from the two placebo-controlled, 6-week studies in adult subjects with schizoaffective disorder, between-group comparisons revealed no medically important differences between INVEGA and placebo in the proportions of subjects experiencing potentially clinically significant changes in routine serum chemistry, hematology, or urinalysis parameters. Similarly, there were no differences between INVEGA and placebo in the incidence of discontinuations due to changes in hematology, urinalysis, or serum chemistry, including mean changes from baseline in fasting glucose, insulin, c-peptide, triglyceride, HDL, LDL, and total cholesterol measurements. However, INVEGA was associated with increases in serum prolactin®®® [see ]. Warnings and Precautions (5.7)

6.9 Other Adverse Reactions Observed During Premarketing Evaluation of INVEGA®

The following additional adverse reactions occurred in < 2% of INVEGA -treated subjects in the above schizophrenia and schizoaffective disorder clinical trial datasets. The following also includes additional adverse reactions reported at any frequency by INVEGA -treated subjects who participated in other clinical studies.®®

bradycardia, palpitations Cardiac disorders:

eye movement disorder Eye disorders:

flatulence Gastrointestinal disorders:

edema General disorders:

anaphylactic reaction Immune system disorders:

urinary tract infection Infections and infestations:

alanine aminotransferase increased, aspartate aminotransferase increased Investigations:

arthralgia, pain in extremity Musculoskeletal and connective tissue disorders:

opisthotonus Nervous system disorders:

agitation, insomnia, nightmare Psychiatric disorders:

breast discomfort, menstruation irregular, retrograde ejaculation Reproductive system and breast disorders:

nasal congestion Respiratory, thoracic and mediastinal disorders:

pruritus, rash Skin and subcutaneous tissue disorders:

hypertension Vascular disorders:

The safety of INVEGA was also evaluated in a long-term trial designed to assess the maintenance of effect with INVEGA in adults with schizophrenia . In general, adverse reaction types, frequencies, and severities during the initial 14-week open-label phase of this study were comparable to those observed in the 6-week, placebo-controlled, fixed-dose studies. Adverse reactions reported during the long-term double-blind phase of this study were similar in type and severity to those observed in the initial 14-week open-label phase.®® [see ] Clinical Studies (14)

6.10 Postmarketing Experience

The following adverse reactions have been identified during postapproval use of INVEGA ; because these reactions were reported voluntarily from a population of uncertain size, it is not possible to reliably estimate their frequency: angioedema, ileus, priapism, swollen tongue, tardive dyskinesia, urinary incontinence, urinary retention.®

6.11 Adverse Reactions Reported With Risperidone

Paliperidone is the major active metabolite of risperidone. Adverse reactions reported with risperidone can be found in the ADVERSE REACTIONS section of the risperidone package insert.

7 DRUG INTERACTIONS

7.1 Potential for INVEGA to Affect Other Drugs®

Given the primary CNS effects of paliperidone , INVEGA should be used with caution in combination with other centrally acting drugs and alcohol. Paliperidone may antagonize the effect of levodopa and other dopamine agonists. [see ,)] Adverse Reactions (6.16.2®

Because of its potential for inducing orthostatic hypotension, an additive effect may be observed when INVEGA is administered with other therapeutic agents that have this potential .® [see ] Warnings and Precautions (5.9)

Paliperidone is not expected to cause clinically important pharmacokinetic interactions with drugs that are metabolized by cytochrome P450 isozymes. studies in human liver microsomes showed that paliperidone does not substantially inhibit the metabolism of drugs metabolized by cytochrome P450 isozymes, including CYP1A2, CYP2A6, CYP2C8/9/10, CYP2D6, CYP2E1, CYP3A4, and CYP3A5. Therefore, paliperidone is not expected to inhibit clearance of drugs that are metabolized by these metabolic pathways in a clinically relevant manner. Paliperidone is also not expected to have enzyme inducing properties. In vitro

Paliperidone is a weak inhibitor of P-glycoprotein (P-gp) at high concentrations. No data are available and the clinical relevance is unknown. in vivo

Pharmacokinetic interaction between lithium and INVEGA is unlikely.®

In a drug interaction study, co-administration of INVEGA (12 mg once daily for 5 days) with divalproex sodium extended-release tablets (500 mg to 2000 mg once daily) did not affect the steady-state pharmacokinetics (AUC and C) of valproate in 13 patients stabilized on valproate. In a clinical study, subjects on stable doses of valproate had comparable valproate average plasma concentrations when INVEGA 3–15 mg/day was added to their existing valproate treatment.®24hmax,ss®

7.2 Potential for Other Drugs to Affect INVEGA®

Paliperidone is not a substrate of CYP1A2, CYP2A6, CYP2C9, and CYP2C19, so that an interaction with inhibitors or inducers of these isozymes is unlikely. While studies indicate that CYP2D6 and CYP3A4 may be minimally involved in paliperidone metabolism, studies do not show decreased elimination by these isozymes and they contribute to only a small fraction of total body clearance. studies have shown that paliperidone is a P-gp substrate. in vitroin vivo In vitro

Co-administration of INVEGA 6 mg once daily with carbamazepine, a strong inducer of both CYP3A4 and P-glycoprotein (P-gp), at 200 mg twice daily caused a decrease of approximately 37% in the mean steady-state C and AUC of paliperidone. This decrease is caused, to a substantial degree, by a 35% increase in renal clearance of paliperidone. A minor decrease in the amount of drug excreted unchanged in the urine suggests that there was little effect on the CYP metabolism or bioavailability of paliperidone during carbamazepine co-administration. On initiation of carbamazepine, the dose of INVEGA should be re-evaluated and increased if necessary. Conversely, on discontinuation of carbamazepine, the dose of INVEGA should be re-evaluated and decreased if necessary.®max®®

Paliperidone is metabolized to a limited extent by CYP2D6 . In an interaction study in healthy subjects in which a single 3 mg dose of INVEGA was administered concomitantly with 20 mg per day of paroxetine (a potent CYP2D6 inhibitor), paliperidone exposures were on average 16% (90% CI: 4, 30) higher in CYP2D6 extensive metabolizers. Higher doses of paroxetine have not been studied. The clinical relevance is unknown. [see ] Clinical Pharmacology (12.3)®

Co-administration of a single dose of INVEGA 12 mg with divalproex sodium extended-release tablets (two 500 mg tablets once daily) resulted in an increase of approximately 50% in the C and AUC of paliperidone. Dosage reduction for INVEGA should be considered when INVEGA is co-administered with valproate after clinical assessment.®max®®

Pharmacokinetic interaction between lithium and INVEGA is unlikely.®

8 USE IN SPECIFIC POPULATIONS

8.1 Pregnancy

TERATOGENIC EFFECTS

. Pregnancy Category C

There are no adequate and well controlled studies of INVEGA in pregnant women.®

Use of first generation antipsychotic drugs during the last trimester of pregnancy has been associated with extrapyramidal symptoms in the neonate. These symptoms are usually self-limited. It is not known whether paliperidone, when taken near the end of pregnancy, will lead to similar neonatal signs and symptoms.

In animal reproduction studies, there were no increases in fetal abnormalities when pregnant rats and rabbits were treated during the period of organogenesis with up to 8 times the maximum recommended human dose of paliperidone (on a mg/m basis).^2

In rat reproduction studies with risperidone, which is extensively converted to paliperidone in rats and humans, there were increases in pup deaths seen at oral doses which are less than the maximum recommended human dose of risperidone on a mg/m basis (see risperidone package insert).^2

Non-teratogenic Effects

Neonates exposed to antipsychotic drugs during the third trimester of pregnancy are at risk for extrapyramidal and/or withdrawal symptoms following delivery. There have been reports of agitation, hypertonia, hypotonia, tremor, somnolence, respiratory distress, and feeding disorder in these neonates. These complications have varied in severity; while in some cases symptoms have been self-limited, in other cases neonates have required intensive care unit support and prolonged hospitalization.

INVEGA should be used during pregnancy only if the potential benefit justifies the potential risk to the fetus.®

8.3 Nursing Mothers

Paliperidone is excreted in human breast milk. The known benefits of breastfeeding should be weighed against the unknown risks of infant exposure to paliperidone.

8.4 Pediatric Use

Safety and effectiveness of INVEGA in the treatment of schizophrenia were evaluated in 150 adolescent subjects 12–17 years of age with schizophrenia who received INVEGA in the dose range of 1.5 mg to 12 mg/day in a 6-week, double-blind, placebo-controlled trial.®®

Safety and effectiveness of INVEGA for the treatment of schizophrenia in patients < 12 years of age have not been established. Safety and effectiveness of INVEGA for the treatment of schizoaffective disorder in patients < 18 years of age have not been studied.®®

In a study in which juvenile rats were treated with oral paliperidone from days 24 to 73 of age, a reversible impairment of performance in a test of learning and memory was seen, in females only, with a no-effect dose of 0.63 mg/kg/day, which produced plasma levels (AUC) of paliperidone similar to those in adolescents. No other consistent effects on neurobehavioral or reproductive development were seen up to the highest dose tested (2.5 mg/kg/day), which produced plasma levels of paliperidone 2–3 times those in adolescents.

Juvenile dogs were treated for 40 weeks with oral risperidone, which is extensively metabolized to paliperidone in animals and humans, at doses of 0.31, 1.25, or 5 mg/kg/day. Decreased bone length and density were seen with a no-effect dose of 0.31 mg/kg/day, which produced plasma levels (AUC) of risperidone plus paliperidone which were similar to those in children and adolescents receiving the maximum recommended human dose of risperidone. In addition, a delay in sexual maturation was seen at all doses in both males and females. The above effects showed little or no reversibility in females after a 12-week drug-free recovery period.

The long-term effects of INVEGA on growth and sexual maturation have not been fully evaluated in children and adolescents.®

8.5 Geriatric Use

The safety, tolerability, and efficacy of INVEGA were evaluated in a 6-week placebo-controlled study of 114 elderly subjects with schizophrenia (65 years of age and older, of whom 21 were 75 years of age and older). In this study, subjects received flexible doses of INVEGA (3 mg to 12 mg once daily). In addition, a small number of subjects 65 years of age and older were included in the 6-week placebo-controlled studies in which adult schizophrenic subjects received fixed doses of INVEGA (3 mg to 15 mg once daily) . There were no subjects ≥ 65 years of age in the schizoaffective disorder studies.®®® [see ] Clinical Studies (14)

Overall, of the total number of subjects in schizophrenia clinical studies of INVEGA (n = 1796), including those who received INVEGA or placebo, 125 (7.0%) were 65 years of age and older and 22 (1.2%) were 75 years of age and older. No overall differences in safety or effectiveness were observed between these subjects and younger subjects, and other reported clinical experience has not identified differences in response between the elderly and younger patients, but greater sensitivity of some older individuals cannot be ruled out.®®

This drug is known to be substantially excreted by the kidney and clearance is decreased in patients with moderate to severe renal impairment , who should be given reduced doses. Because elderly patients are more likely to have decreased renal function, care should be taken in dose selection, and it may be useful to monitor renal function . [see ] Clinical Pharmacology (12.3) [see ] Dosage and Administration (2.5)

8.6 Renal Impairment

Dosing must be individualized according to the patient's renal function status . [see ] Dosage and Administration (2.5)

8.7 Hepatic Impairment

No dosage adjustment is required in patients with mild to moderate hepatic impairment. INVEGA has not been studied in patients with severe hepatic impairment.®

9 DRUG ABUSE AND DEPENDENCE

9.1 Controlled Substance

INVEGA (paliperidone) is not a controlled substance.®

9.2 Abuse

Paliperidone has not been systematically studied in animals or humans for its potential for abuse. It is not possible to predict the extent to which a CNS-active drug will be misused, diverted, and/or abused once marketed. Consequently, patients should be evaluated carefully for a history of drug abuse, and such patients should be observed closely for signs of INVEGA misuse or abuse (e.g., development of tolerance, increases in dose, drug-seeking behavior).®

9.3 Dependence

Paliperidone has not been systematically studied in animals or humans for its potential for tolerance or physical dependence.

10 OVERDOSAGE

10.1 Human Experience

While experience with paliperidone overdose is limited, among the few cases of overdose reported in pre-marketing trials, the highest estimated ingestion of INVEGA was 405 mg. Observed signs and symptoms included extrapyramidal symptoms and gait unsteadiness. Other potential signs and symptoms include those resulting from an exaggeration of paliperidone's known pharmacological effects, i.e., drowsiness and somnolence, tachycardia and hypotension, and QT prolongation. Torsade de pointes and ventricular fibrillation have been reported in a patient in the setting of overdose.®

Paliperidone is the major active metabolite of risperidone. Overdose experience reported with risperidone can be found in the OVERDOSAGE section of the risperidone package insert.

10.2 Management of Overdosage

There is no specific antidote to paliperidone, therefore, appropriate supportive measures should be instituted and close medical supervision and monitoring should continue until the patient recovers. Consideration should be given to the extended-release nature of the product when assessing treatment needs and recovery. Multiple drug involvement should also be considered.

In case of acute overdose, establish and maintain an airway and ensure adequate oxygenation and ventilation. Gastric lavage (after intubation if patient is unconscious) and administration of activated charcoal together with a laxative should be considered.

The possibility of obtundation, seizures, or dystonic reaction of the head and neck following overdose may create a risk of aspiration with induced emesis.

Cardiovascular monitoring should commence immediately, including continuous electrocardiographic monitoring for possible arrhythmias. If antiarrhythmic therapy is administered, disopyramide, procainamide, and quinidine carry a theoretical hazard of additive QT-prolonging effects when administered in patients with an acute overdose of paliperidone. Similarly the alpha-blocking properties of bretylium might be additive to those of paliperidone, resulting in problematic hypotension.

Hypotension and circulatory collapse should be treated with appropriate measures, such as intravenous fluids and/or sympathomimetic agents (epinephrine and dopamine should not be used, since beta stimulation may worsen hypotension in the setting of paliperidone-induced alpha blockade). In cases of severe extrapyramidal symptoms, anticholinergic medication should be administered.

11 DESCRIPTION

Paliperidone, the active ingredient in INVEGA Extended-Release Tablets, is a psychotropic agent belonging to the chemical class of benzisoxazole derivatives. INVEGA contains a racemic mixture of (+)- and (-)- paliperidone. The chemical name is (±)-3-[2-[4-(6-fluoro-1,2-benzisoxazol-3-yl)-1-piperidinyl]ethyl]-6,7,8,9-tetrahydro-9-hydroxy-2-methyl-4H-pyrido[1,2-a]pyrimidin-4-one. Its molecular formula is C H FN O and its molecular weight is 426.49. The structural formula is:®®232743

Paliperidone is sparingly soluble in 0.1N HCl and methylene chloride; practically insoluble in water, 0.1N NaOH, and hexane; and slightly soluble in N,N-dimethylformamide.

INVEGA (paliperidone) Extended-Release Tablets are available in 1.5 mg (orange-brown), 3 mg (white), 6 mg (beige), and 9 mg (pink) strengths. INVEGA utilizes OROS osmotic drug-release technology .®®® [see ] Description (11.1)

Inactive ingredients are carnauba wax, cellulose acetate, hydroxyethyl cellulose, propylene glycol, polyethylene glycol, polyethylene oxides, povidone, sodium chloride, stearic acid, butylated hydroxytoluene, hypromellose, titanium dioxide, and iron oxides. The 3 mg tablets also contain lactose monohydrate and triacetin.

11.1 Delivery System Components and Performance

INVEGA uses osmotic pressure to deliver paliperidone at a controlled rate. The delivery system, which resembles a capsule-shaped tablet in appearance, consists of an osmotically active trilayer core surrounded by a subcoat and semipermeable membrane. The trilayer core is composed of two drug layers containing the drug and excipients, and a push layer containing osmotically active components. There are two precision laser-drilled orifices on the drug-layer dome of the tablet. Each tablet strength has a different colored water-dispersible overcoat and print markings. In an aqueous environment, such as the gastrointestinal tract, the water-dispersible color overcoat erodes quickly. Water then enters the tablet through the semipermeable membrane that controls the rate at which water enters the tablet core, which, in turn, determines the rate of drug delivery. The hydrophilic polymers of the core hydrate and swell, creating a gel containing paliperidone that is then pushed out through the tablet orifices. The biologically inert components of the tablet remain intact during gastrointestinal transit and are eliminated in the stool as a tablet shell, along with insoluble core components.®

12 CLINICAL PHARMACOLOGY

12.1 Mechanism of Action

Paliperidone is the major active metabolite of risperidone. The mechanism of action of paliperidone, as with other drugs having efficacy in schizophrenia, is unknown, but it has been proposed that the drug's therapeutic activity in schizophrenia is mediated through a combination of central dopamine Type 2 (D) and serotonin Type 2 (5HT) receptor antagonism.22A

12.2 Pharmacodynamics

Paliperidone is a centrally active dopamine Type 2 (D) antagonist and with predominant serotonin Type 2 (5HT) activity. Paliperidone is also active as an antagonist at α and α adrenergic receptors and H histaminergic receptors, which may explain some of the other effects of the drug. Paliperidone has no affinity for cholinergic muscarinic or β - and β -adrenergic receptors. The pharmacological activity of the (+)- and (-)- paliperidone enantiomers is qualitatively and quantitatively similar22A12112 in vitro.

12.3 Pharmacokinetics

Following a single dose, the plasma concentrations of paliperidone gradually rise to reach peak plasma concentration (C) approximately 24 hours after dosing. The pharmacokinetics of paliperidone following INVEGA administration are dose-proportional within the available dose range. The terminal elimination half-life of paliperidone is approximately 23 hours.max®

Steady-state concentrations of paliperidone are attained within 4–5 days of dosing with INVEGA in most subjects. The mean steady-state peak:trough ratio for an INVEGA dose of 9 mg was 1.7 with a range of 1.2–3.1.®®

Following administration of INVEGA , the (+) and (-) enantiomers of paliperidone interconvert, reaching an AUC (+) to (-) ratio of approximately 1.6 at steady state.®

Absorption and Distribution

The absolute oral bioavailability of paliperidone following INVEGA administration is 28%.®

Administration of a 12 mg paliperidone extended-release tablet to healthy ambulatory subjects with a standard high-fat/high-caloric meal gave mean C and AUC values of paliperidone that were increased by 60% and 54%, respectively, compared with administration under fasting conditions. Clinical trials establishing the safety and efficacy of INVEGA were carried out in subjects without regard to the timing of meals. While INVEGA can be taken without regard to food, the presence of food at the time of INVEGA administration may increase exposure to paliperidone .max®®® [see ] Dosage and Administration (2.3)

Based on a population analysis, the apparent volume of distribution of paliperidone is 487 L. The plasma protein binding of racemic paliperidone is 74%.

Metabolism and Elimination

Although studies suggested a role for CYP2D6 and CYP3A4 in the metabolism of paliperidone, results indicate that these isozymes play a limited role in the overall elimination of paliperidone . in vitroin vivo [see ] Drug Interactions (7)

One week following administration of a single oral dose of 1 mg immediate-release C-paliperidone to 5 healthy volunteers, 59% (range 51% – 67%) of the dose was excreted unchanged into urine, 32% (26% – 41%) of the dose was recovered as metabolites, and 6% – 12% of the dose was not recovered. Approximately 80% of the administered radioactivity was recovered in urine and 11% in the feces. Four primary metabolic pathways have been identified , none of which could be shown to account for more than 10% of the dose: dealkylation, hydroxylation, dehydrogenation, and benzisoxazole scission.^14 in vivo

Population pharmacokinetic analyses found no difference in exposure or clearance of paliperidone between extensive metabolizers and poor metabolizers of CYP2D6 substrates.

Special Populations

Renal Impairment

The dose of INVEGA should be reduced in patients with moderate or severe renal impairment . The disposition of a single dose paliperidone 3 mg extended-release tablet was studied in adult subjects with varying degrees of renal function. Elimination of paliperidone decreased with decreasing estimated creatinine clearance. Total clearance of paliperidone was reduced in subjects with impaired renal function by 32% on average in mild (CrCl = 50 mL/min to < 80 mL/min), 64% in moderate (CrCl = 30 mL/min to < 50 mL/min), and 71% in severe (CrCl = 10 mL/min to < 30 mL/min) renal impairment, corresponding to an average increase in exposure (AUCinf) of 1.5 fold, 2.6 fold, and 4.8 fold, respectively, compared to healthy subjects. The mean terminal elimination half-life of paliperidone was 24 hours, 40 hours, and 51 hours in subjects with mild, moderate, and severe renal impairment, respectively, compared with 23 hours in subjects with normal renal function (CrCl ≥ 80 mL/min).® [see ] Dosage and Administration (2.5)

Hepatic Impairment

In a study in adult subjects with moderate hepatic impairment (Child-Pugh class B), the plasma concentrations of free paliperidone were similar to those of healthy subjects, although total paliperidone exposure decreased because of a decrease in protein binding. Consequently, no dose adjustment is required in patients with mild or moderate hepatic impairment. INVEGA has not been studied in patients with severe hepatic impairment.®

Adolescents (12–17 years of age)

Paliperidone systemic exposure in adolescents weighing ≥ 51 kg (≥ 112 lbs) was similar to that in adults. In adolescents weighing < 51 kg (< 112 lbs), a 23% higher exposure was observed; this is considered not to be clinically significant. Age did not influence the paliperidone exposure.

Elderly

No dosage adjustment is recommended based on age alone. However, dose adjustment may be required because of age-related decreases in creatinine clearance . [see above and ,)] Renal Impairment Dosage and Administration (2.12.5

Race

No dosage adjustment is recommended based on race. No differences in pharmacokinetics were observed in a pharmacokinetic study conducted in Japanese and Caucasians.

Gender

No dosage adjustment is recommended based on gender. No differences in pharmacokinetics were observed in a pharmacokinetic study conducted in men and women.

Smoking

No dosage adjustment is recommended based on smoking status. Based on in vitro studies utilizing human liver enzymes, paliperidone is not a substrate for CYP1A2; smoking should, therefore, not have an effect on the pharmacokinetics of paliperidone.

13 NONCLINICAL TOXICOLOGY

13.1 Carcinogenesis, Mutagenesis, Impairment of Fertility

Carcinogenesis

Carcinogenicity studies of paliperidone have not been performed.

Carcinogenicity studies of risperidone, which is extensively converted to paliperidone in rats, mice, and humans, were conducted in Swiss albino mice and Wistar rats. Risperidone was administered in the diet at daily doses of 0.63 mg/kg, 2.5 mg/kg, and 10 mg/kg for 18 months to mice and for 25 months to rats. A maximum tolerated dose was not achieved in male mice. There were statistically significant increases in pituitary gland adenomas, endocrine pancreas adenomas, and mammary gland adenocarcinomas. The no-effect dose for these tumors was less than or equal to the maximum recommended human dose of risperidone on a mg/m2 basis (see risperidone package insert). An increase in mammary, pituitary, and endocrine pancreas neoplasms has been found in rodents after chronic administration of other antipsychotic drugs and is considered to be mediated by prolonged dopamine D2 antagonism and hyperprolactinemia. The relevance of these tumor findings in rodents in terms of human risk is unknown . [see ] Warnings and Precautions (5.7)

Mutagenesis

No evidence of genotoxic potential for paliperidone was found in the Ames reverse mutation test, the mouse lymphoma assay, or the rat micronucleus test. in vivo

Impairment of Fertility

In a study of fertility, the percentage of treated female rats that became pregnant was not affected at oral doses of paliperidone of up to 2.5 mg/kg/day. However, pre- and post-implantation loss was increased, and the number of live embryos was slightly decreased, at 2.5 mg/kg, a dose that also caused slight maternal toxicity. These parameters were not affected at a dose of 0.63 mg/kg, which is half of the maximum recommended human dose on a mg/m basis.^2

The fertility of male rats was not affected at oral doses of paliperidone of up to 2.5 mg/kg/day, although sperm count and sperm viability studies were not conducted with paliperidone. In a subchronic study in Beagle dogs with risperidone, which is extensively converted to paliperidone in dogs and humans, all doses tested (0.31 mg/kg – 5.0 mg/kg) resulted in decreases in serum testosterone and in sperm motility and concentration. Serum testosterone and sperm parameters partially recovered, but remained decreased after the last observation (two months after treatment was discontinued).

14 CLINICAL STUDIES

14.1 Schizophrenia

Adults

The acute efficacy of INVEGA (3 mg to 15 mg once daily) was established in three placebo-controlled and active-controlled (olanzapine), 6-week, fixed-dose trials in non-elderly adult subjects (mean age of 37) who met DSM-IV criteria for schizophrenia. Studies were carried out in North America, Eastern Europe, Western Europe, and Asia. The doses studied among these three trials included 3 mg/day, 6 mg/day, 9 mg/day, 12 mg/day, and 15 mg/day. Dosing was in the morning without regard to meals.®

Efficacy was evaluated using the Positive and Negative Syndrome Scale (PANSS), a validated multi-item inventory composed of five factors to evaluate positive symptoms, negative symptoms, disorganized thoughts, uncontrolled hostility/excitement, and anxiety/depression. Efficacy was also evaluated using the Personal and Social Performance (PSP) scale. The PSP is a validated clinician-rated scale that measures personal and social functioning in the domains of socially useful activities (e.g., work and study), personal and social relationships, self-care, and disturbing and aggressive behaviors.

In all 3 studies (n = 1665), INVEGA was superior to placebo on the PANSS at all doses. Mean effects at all doses were fairly similar, although the higher doses in all studies were numerically superior. INVEGA was also superior to placebo on the PSP in these trials.®®

An examination of population subgroups did not reveal any evidence of differential responsiveness on the basis of gender, age (there were few patients over 65), or geographic region. There were insufficient data to explore differential effects based on race.

In a longer-term trial, adult outpatients meeting DSM-IV criteria for schizophrenia who had clinically responded (defined as PANSS score ≤ 70 or ≤ 4 on pre-defined PANSS subscales, as well as having been on a stable fixed dose of INVEGA for the last two weeks of an 8-week run-in phase) were entered into a 6-week open-label stabilization phase where they received INVEGA (doses ranging from 3 mg to 15 mg once daily). After the stabilization phase, patients were randomized in a double-blind manner to either continue on INVEGA at their achieved stable dose, or to placebo, until they experienced a relapse of schizophrenia symptoms. Relapse was pre-defined as significant increase in PANSS (or pre-defined PANSS subscales), hospitalization, clinically significant suicidal or homicidal ideation, or deliberate injury to self or others. An interim analysis of the data showed a significantly longer time to relapse in patients treated with INVEGA compared to placebo, and the trial was stopped early because maintenance of efficacy was demonstrated.®®®®

Adolescents

The efficacy of INVEGA in adolescent subjects with schizophrenia was established in a randomized, double-blind, parallel-group, placebo-controlled, 6-week study using a fixed-dose weight-based treatment group design over the dose range of 1.5 to 12 mg/day. The study was carried out in the US, India, Romania, Russia, and Ukraine, and involved subjects 12–17 years of age meeting DSM-IV criteria for schizophrenia, with diagnosis confirmation using the Kiddie Schedule for Affective Disorders and Schizophrenia-Present and Lifetime Version (K-SADS-PL).®

Eligible subjects were randomly assigned to 1 of 4 treatment groups: a placebo group or INVEGA Low, Medium, or High dose groups. Doses were administered based on body weight to minimize the risk of exposing lower-weight adolescents to high doses of INVEGA . Subjects weighing between 29 kg and less than 51 kg at the baseline visit were randomly assigned to receive placebo or 1.5 mg (Low dose), 3 mg (Medium dose), or 6 mg (High dose) of INVEGA daily, and subjects weighing at least 51 kg at the baseline visit were randomly assigned to receive placebo or 1.5 mg (Low dose), 6 mg (Medium dose), or 12 mg (High dose) of INVEGA daily. Dosing was in the morning without regard to meals.®®®®

Efficacy was evaluated using PANSS. Overall, this study demonstrated the efficacy of INVEGA in adolescents with schizophrenia in the dose range of 3 to 12 mg/day. Doses within this broad range were shown to be effective, however, there was no clear enhancement to efficacy at the higher doses, i.e., 6 mg for subjects weighing less than 51 kg and 12 mg for subjects weighing 51 kg or greater. Although paliperidone was adequately tolerated within the dose range of 3 to 12 mg/day, adverse events were dose related.®

14.2 Schizoaffective Disorder

Adults

The acute efficacy of INVEGA (3 mg to 12 mg once daily) in the treatment of schizoaffective disorder was established in two placebo-controlled, 6-week trials in non-elderly adult subjects. Enrolled subjects 1) met DSM-IV criteria for schizoaffective disorder, as confirmed by the Structured Clinical Interview for DSM-IV Disorders, 2) had a Positive and Negative Syndrome Scale (PANSS) total score of at least 60, and 3) had prominent mood symptoms as confirmed by a score of at least 16 on the Young Mania Rating Scale and/or Hamilton Rating Scale for Depression. The population included subjects with schizoaffective bipolar and depressive types. In one of these trials, efficacy was assessed in 211 subjects who received flexible doses of INVEGA (3–12 mg once daily). In the other study, efficacy was assessed in 203 subjects who were assigned to one of two dose levels of INVEGA : 6 mg with the option to reduce to 3 mg (n = 105) or 12 mg with the option to reduce to 9 mg (n = 98) once daily. Both studies included subjects who received INVEGA either as monotherapy [no mood stabilizers and/or antidepressants (55%)] or as an adjunct to mood stabilizers and/or antidepressants (45%). The most commonly used mood stabilizers were valproate and lithium. The most commonly used antidepressants were SSRIs and SNRIs. INVEGA was dosed in the morning without regard to meals. Studies were carried out in the United States, Eastern Europe, Russia, and Asia.®®®®®

Efficacy was evaluated using the PANSS, a validated multi-item inventory composed of five factors to evaluate positive symptoms, negative symptoms, disorganized thoughts, uncontrolled hostility/excitement, and anxiety/depression. As secondary outcomes, mood symptoms were evaluated using the Hamilton Depression Rating Scale (HAM-D-21) and the Young Mania Rating Scale (YMRS).

The INVEGA group in the flexible-dose study (dosed between 3 and 12 mg/day, mean modal dose of 8.6 mg/day) and the higher dose group of INVEGA in the 2 dose-level study (12 mg/day with option to reduce to 9 mg/day) were each superior to placebo in the PANSS. Numerical improvements in mood symptoms were also observed, as measured by the HAM-D-21 and YMRS. In the lower dose group of the 2 dose-level study (6 mg/day with option to reduce to 3 mg/day), INVEGA was not significantly different from placebo as measured by the PANSS.®®®

Taking the results of both studies together, INVEGA improved the symptoms of schizoaffective disorder at endpoint relative to placebo when administered either as monotherapy or as an adjunct to mood stabilizers and/or antidepressants. An examination of population subgroups did not reveal any evidence of differential responsiveness on the basis of gender, age, or geographic region. There were insufficient data to explore differential effects based on race.®

16 HOW SUPPLIED/STORAGE AND HANDLING

NDC:64725-0550-1 in a BOTTLE of 30 TABLET, EXTENDED RELEASES

Storage and Handling

Store up to 25°C (77°F); excursions permitted to 15 – 30°C (59 – 86°F) [see USP Controlled Room Temperature]. Protect from moisture.

Keep out of reach of children.

17 PATIENT COUNSELING INFORMATION

Physicians are advised to discuss the following issues with patients for whom they prescribe INVEGA .®

17.1 Orthostatic Hypotension

Patients should be advised that there is risk of orthostatic hypotension, particularly at the time of initiating treatment, re-initiating treatment, or increasing the dose . [see ] Warnings and Precautions (5.9)

17.2 Interference with Cognitive and Motor Performance

As INVEGA has the potential to impair judgment, thinking, or motor skills, patients should be cautioned about operating hazardous machinery, including automobiles, until they are reasonably certain that INVEGA therapy does not affect them adversely .®® [see ] Warnings and Precautions (5.11)

17.3 Pregnancy

Patients should be advised to notify their physician if they become pregnant or intend to become pregnant during treatment with INVEGA .® [see ] Use in Specific Populations (8.1)

17.4 Nursing

Caution should be exercised when INVEGA is administered to a nursing woman. The known benefits of breastfeeding should be weighed against the unknown risks of infant exposure to paliperidone. .® [See ] Use in Specific Populations (8.3)

17.5 Concomitant Medication

Patients should be advised to inform their physicians if they are taking, or plan to take, any prescription or over-the-counter drugs, as there is a potential for interactions . [see ] Drug Interactions (7)

17.6 Alcohol

Patients should be advised to avoid alcohol while taking INVEGA .® [see ] Drug Interactions (7.1)

17.7 Heat Exposure and Dehydration

Patients should be advised regarding appropriate care in avoiding overheating and dehydration . [see ] Warnings and Precautions (5.17)

17.8 Administration

Patients should be informed that INVEGA should be swallowed whole with the aid of liquids. Tablets should not be chewed, divided, or crushed. The medication is contained within a nonabsorbable shell designed to release the drug at a controlled rate. The tablet shell, along with insoluble core components, is eliminated from the body; patients should not be concerned if they occasionally notice something that looks like a tablet in their stool .® [see ] Dosage and Administration (2.3)

INVEGA (paliperidone) Extended-Release Tablets®

Product of Ireland

Manufactured by: ALZA Corporation Vacaville, CA 95688 OR Janssen Cilag Manufacturing, LLC Gurabo, Puerto Rico 00778

Manufactured for: Janssen Pharmaceuticals, Inc. Titusville, NJ 08560

OROS is a registered trademark of ALZA Corporation

©Janssen Pharmaceuticals, Inc. 2007